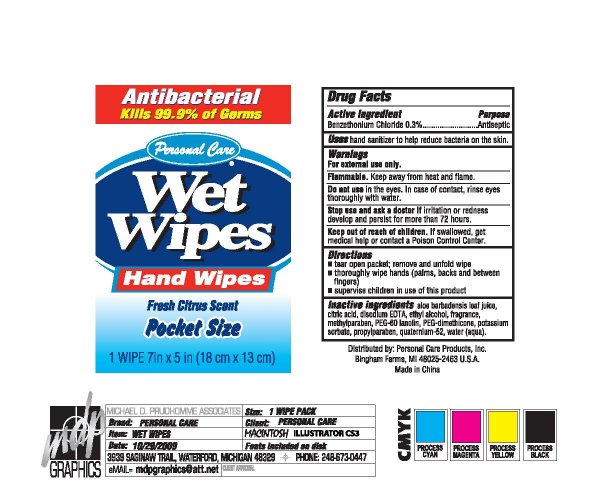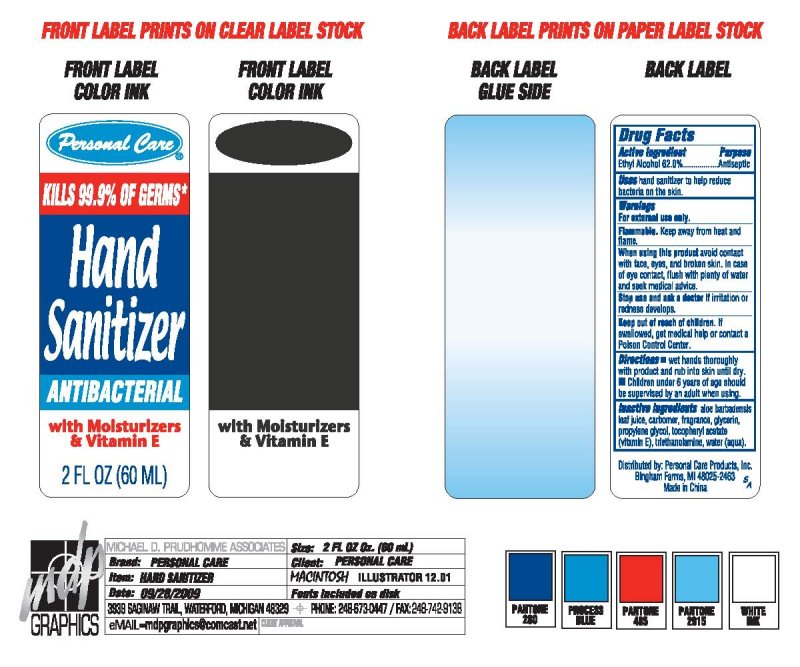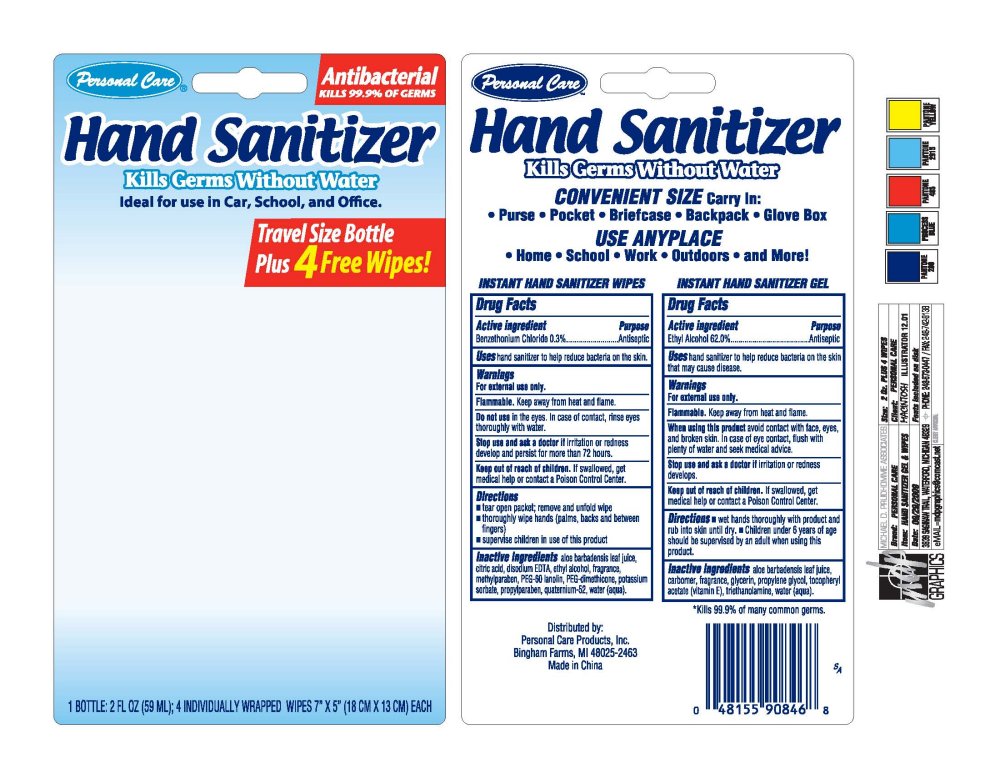 DRUG LABEL: Personal Care
NDC: 29500-1000 | Form: KIT | Route: TOPICAL
Manufacturer: Personal Care Products, Inc.
Category: otc | Type: HUMAN OTC DRUG LABEL
Date: 20091016

ACTIVE INGREDIENTS: ALCOHOL 0.62 mL/1 mL; BENZETHONIUM CHLORIDE 0.003 mL/1 1
INACTIVE INGREDIENTS: ALOE VERA LEAF; CARBOMER HOMOPOLYMER TYPE C; GLYCERIN; PROPYLENE GLYCOL; ALPHA-TOCOPHEROL ACETATE; TROLAMINE; WATER; ALOE VERA LEAF; CITRIC ACID MONOHYDRATE; EDETATE DISODIUM; ALCOHOL; METHYLPARABEN; LANOLIN; DIMETHICONE; POTASSIUM SORBATE; PROPYLPARABEN; WATER

Personal Care Hand Sanitizer Kit

PACKAGE LABEL

Personal Care

Antibacterial

Kills 99.9 percent of Germs

Hand Sanitizer

Kills Germs Without Water

Ideal for use in Car, School, and Office.

Travel Size Bottle

Plus 4 Free Wipes

1 Bottle: 2 FL OZ 59 ML

4 Individually Wrapped Wipes 7 inches X 5 inches 18 CM X 13 CM Each

PACKAGE LABEL

Personal Care

Hand Sanitizer

Kills Germs Without Water

Convenient Size Carry in:

Purse

Pocket

Briefcase

Backpack

Glove Box

Use Anyplace

Home

School

Work Outdoors

and More

Instant Hand Sanitizer Wipes Instant Hand Sanitizer Gel

Distributed by:

Personal Care Products, Inc.

Bingham Farms, MI 48025-2463

Made in China

Kills 99.9 percent of many common germs.

Drug Facts

Active Ingredient Purpose

Ethyl Alcohol 62.0 percent Antiseptic

PURPOSE

Uses hand sanitizer to help reduce bacteria on the skin.

Warnings
For external use only.

SAFE HANDLING WARNING

Flammable. Keep away from heat and flame.

When using this product avoid contact with face, eyes, and broken skin.
In case of eye contact, flush with plenty of water and seek medical advice.

Stop use and ask a doctor if irritation or redness develops.

Keep out of the reach of children.

If swallowed, get medical help or contact a Poison Control Center.

Directions

Wet hands thoroughly with product and rub into skin until dry.

Children under 6 years of age should be supervised by an adult when using.

Inactive ingredients

aloe barbadensis leaf juice, carbomer, fragrance, glycerin,

propylene glycol, tocopheryl acetate vitamin E, triethanolamine, water aqua

Drug Facts

Active Ingredient Purpose

Benzethonium Chloride 0.3 percent Antiseptic

Do not use in the eyes.

In case of contact, rinse eyes thoroughly with water.

Stop use and ask a doctor if irritation or redness develop and persist for more than 72 hours.

Directions

Tear open packet, remove and unfold wipe

Thoroughly wipe hands (palms, backs and between fingers)

Supervise children in use of this product

Inactive ingredients

aloe barbadensis leaf juice, citric acid, disodium EDTA , ethyl alcohol,

fragrance, methylparaben, PEG 60 lanolin, PEG dimethicone, potassium sorbate,

propylparaben, quaternium 52, water aqua